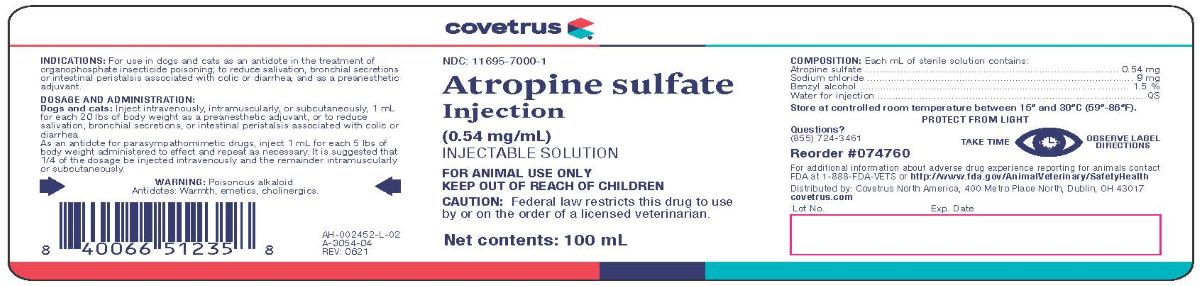 DRUG LABEL: ATROPINE SULFATE 
NDC: 11695-7000 | Form: INJECTION, SOLUTION
Manufacturer: Covetrus North America
Category: animal | Type: PRESCRIPTION ANIMAL DRUG LABEL
Date: 20210701

ACTIVE INGREDIENTS: ATROPINE SULFATE 0.54 mg/1 mL

ATROPINE SULFATE Injections

INDICATIONS AND USAGE

(0.54 mg/mL)

FOR ANIMAL USE ONLY

KEEP OUT OF REACH OF CHILDREN

CAUTION: Federal law restricts this drug to use by or on the order of a licensed veterinarian.

INDICATIONS

For use in Dogs and Cats as an antidote in the treatment of organophosphate insecticide poisoning; to reduce salivation, bronchial secretions or intestinal peristalsis associated with colic or diarrhea, and as a preanesthetic adjuvant.

DOSAGE AND ADMINISTRATION:

Dogs and Cats: Inject intravenously, intramuscularly, or subcutaneously, 1 mL for each 20 lbs of body weight as a preanesthetic adjuvant, or to reudce salivation, bronchial secretions, or intestinal peristalsis associated with colic or diarrhea.

As an antidote for parasympathomimetic drugs, inject 1 mL for each 5 lbs of body weight administered to effect and repeat as necessary. It is suggested that 1/4 of the dosage be injected intravenously and the remainder intramuscularly or subcutaneously.

WARNING

Poisonous alkaloid.

Antidotes: Warmth, emetics, cholinergics

COMPOSITION

Each mL of sterile solution contains:

Atropine Sulfate ............................ 0.54 mg
Sodium Chloride ................................. 9 mg
Benzyl Alcohol .................................. 1.5%
Water for Injection ................................ QS

STORAGE AND HANDLING

Store at controlled room temperature between 15o and 30oC (59o-86oF)

PROTECT FROM LIGHT

TAKE TIME OBSERVE LABEL DIRECTIONS